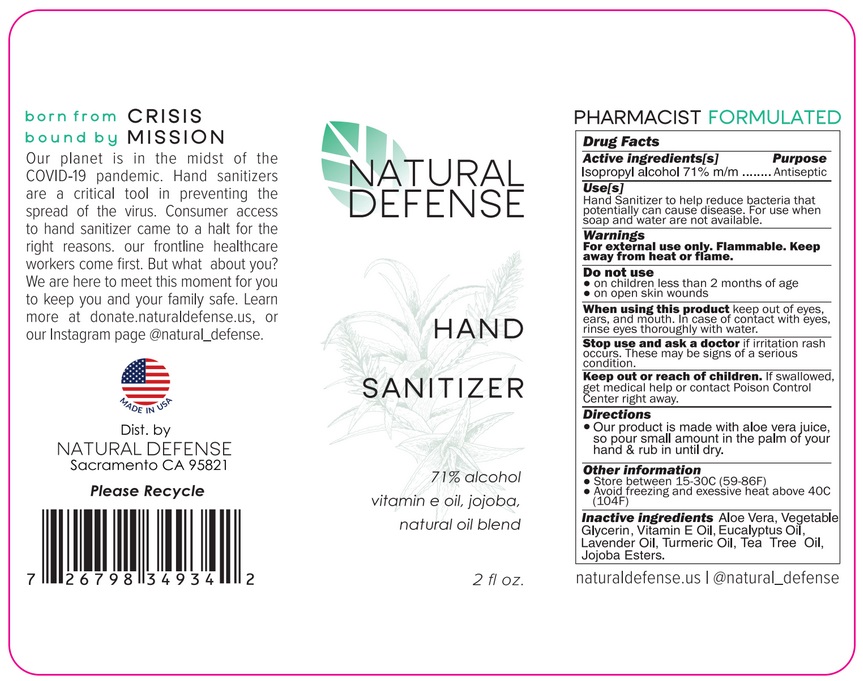 DRUG LABEL: Natural Defense Hand Sanitizer
NDC: 80004-002 | Form: LIQUID
Manufacturer: Grove Inc.
Category: otc | Type: HUMAN OTC DRUG LABEL
Date: 20200808

ACTIVE INGREDIENTS: ISOPROPYL ALCOHOL 71 mL/100 mL
INACTIVE INGREDIENTS: ALOE VERA LEAF; GLYCERIN; .ALPHA.-TOCOPHEROL; EUCALYPTUS OIL; LAVENDER OIL; TURMERIC OIL; TEA TREE OIL; HYDROLYZED JOJOBA ESTERS (ACID FORM)

Active Ingredient

Isopropyl alcohol 71% v/v

Purpose

Antiseptic

Use

Hand Sanitizer to help reduce bacteria that potentially can cause disease. For use when soap and water are not available.

Warnings

For external use only. Flammable. Keep away from heat or flame

Do not use

- in children less than 2 months of age
- on open skin wounds

When using this product keep out of eyes, ears, and mouth. In case of contact with eyes, rinse eyes thoroughly with water.

Stop use and ask a doctor if irritation or rash occurs. These may be signs of a serious condition.

Keep out of reach of children. If swallowed, get medical help or contact a Poison Control Center right away.

Directions

Our product is made with aloe vera juice, so pour small amount in the palm of your hand & rub in until dry.

Other information

- Store between 15-30C (59-86F)
- Avoid freezing and excessive heat above 40C (104F)

Inactive ingredients

Aloe Vera, Vegetable Glycerin, Vitamin E Oil, Eucalyptus Oil, Lavender Oil, Turmeric Oil, Tea Tree Oil, Jojoba Esters